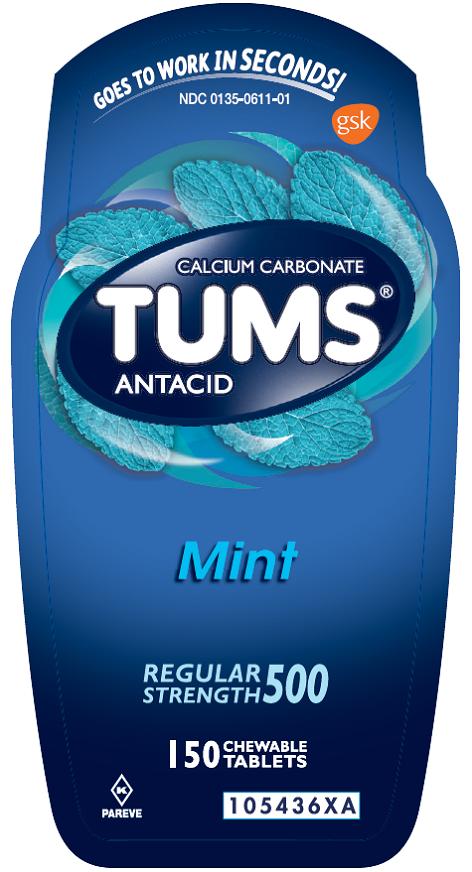 DRUG LABEL: Tums

NDC: 0135-0611 | Form: TABLET, CHEWABLE
Manufacturer: Haleon US Holdings LLC
Category: otc | Type: HUMAN OTC DRUG LABEL
Date: 20240303

ACTIVE INGREDIENTS: CALCIUM CARBONATE 500 mg/1 1
INACTIVE INGREDIENTS: POWDERED CELLULOSE; DEXTROSE, UNSPECIFIED FORM; MALTODEXTRIN; MINERAL OIL; POLYETHYLENE GLYCOL, UNSPECIFIED; TALC

Drug Facts

Active ingredient (per tablet)

Calcium Carbonate USP 500mg

Purpose

Antacid

Uses

relieves

- heartburn
- acid indigestion
- sour stomach
- upset stomach associated with these symptoms

Warnings

Ask a doctor or pharmacist before use if you are

presently taking a prescription drug. Antacids may interact with certain prescription drugs.

When using this product

- do not take more than 15 tablets in 24 hours
- if pregnant do not take more than 10 tablets in 24 hours
- do not use the maximum dosage for more than 2 weeks except under the advice and supervision of a doctor

Keep out of reach of children.

Click here to enter Precautions

Directions

- adults and children 12 years of age and over:chew 2-4 tablets as symptoms occur, or as directed by a doctor
- do not take for symptoms that persist for more than 2 weeks unless advised by a doctor

Other information

- each chewable tablet contains:elemental calcium 200 mg
- do not store above 25°C (77°F)

Inactive ingredients

cellulose, dextrose, flavor, maltodextrin, mineral oil, polyethylene glycol, talc

Questions?

1-800-897-7535

Principal Display Panel

NDC 0135-0611-01

TUMS®

ANTACID

CALCIUM CARBONATE

GOES TO WORK IN SECONDS!

Mint

REGULARE STRENGTH 500

150 CHEWABLE TABLETS

PAREVE

Safety sealed – Do not use if printed inner seal beneath cap is missing or broken.

Trademarks are owned by or licensed to the GSK group of companies.

Dist. by:

GSKConsumer Healthcare

Warren, NJ 07059

©2014 GSK or its licensor

Front Label: 105436XA

Back Label: 105437XA